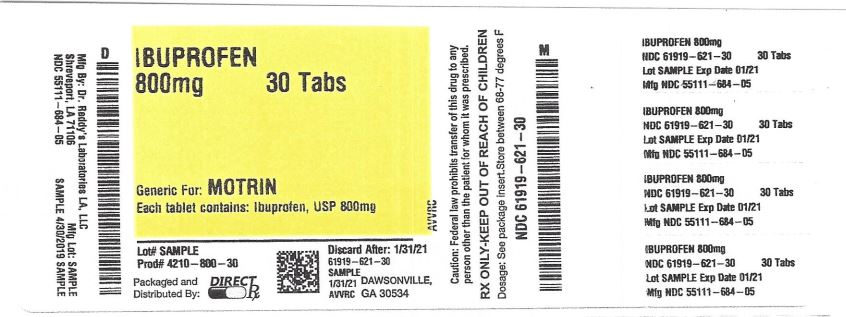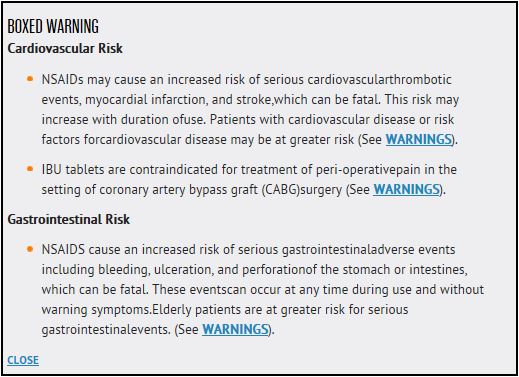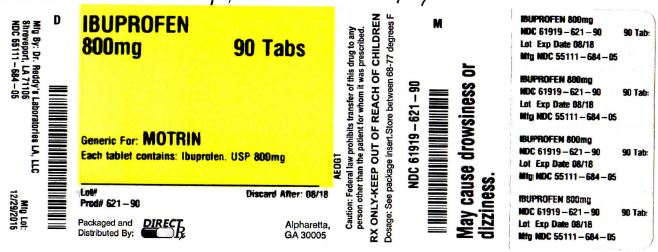 DRUG LABEL: IBU
NDC: 61919-621 | Form: TABLET
Manufacturer: DirectRX
Category: prescription | Type: HUMAN PRESCRIPTION DRUG LABEL
Date: 20190502

ACTIVE INGREDIENTS: IBUPROFEN 800 mg/1 1
INACTIVE INGREDIENTS: POLYSORBATE 80; POLYETHYLENE GLYCOL, UNSPECIFIED; TITANIUM DIOXIDE; CARNAUBA WAX; SILICON DIOXIDE; CROSCARMELLOSE SODIUM; HYPROMELLOSES; MAGNESIUM STEARATE; CELLULOSE, MICROCRYSTALLINE; POLYDEXTROSE

IBU